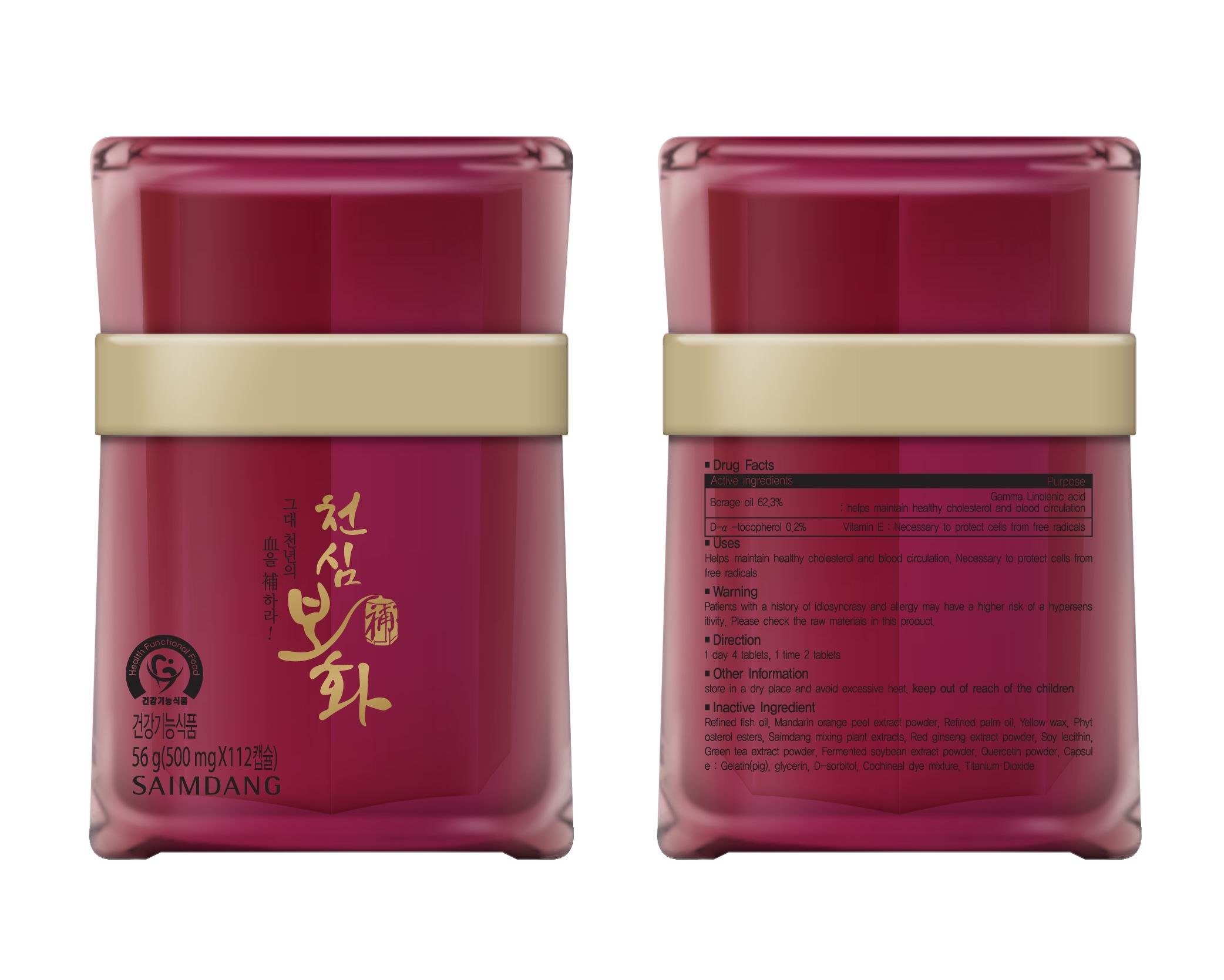 DRUG LABEL: Cheon Shim Bo Hwa
NDC: 51220-5001 | Form: CAPSULE
Manufacturer: Saimdang Cosmetics Co., Ltd
Category: otc | Type: HUMAN OTC DRUG LABEL
Date: 20110406

ACTIVE INGREDIENTS: BORAGE OIL 311 mg/1 1; .ALPHA.-TOCOPHEROL ACETATE, D- 1 mg/1 1
INACTIVE INGREDIENTS: FISH OIL; MANDARIN OIL; PALM OIL; YELLOW WAX; ASIAN GINSENG; LECITHIN, SOYBEAN; GREEN TEA LEAF; SOYBEAN; QUERCETIN; GELATIN; GLYCERIN; SORBITOL; TITANIUM DIOXIDE; GARDENIA JASMINOIDES FRUIT; COCHINEAL

Drug Facts

Active ingredient: Borage oil, D Alpha Tocopherol

Inactive ingredient: fish oil, mandarin orange peel extract powder, palm oil, yellow wax, red ginseng extract powder, soy lecithin, green tea extract, soybean extract, quercetin powder, gelatin, glycerin, D-sorbitol, cochineal, titanium dioxide

DOSAGE AND ADMINISTRATION

1 day 4 tablets, 1 time 2 tablets

INDICATIONS AND USAGE

necessary to protect cells from free radicals

keep out of reach of children

PURPOSE

helps maintain healthy chlesterol and blood circulation

WARNINGS

patients with a history of idiosyncrasy and allergy may have a higher risk of a hypersensitivity